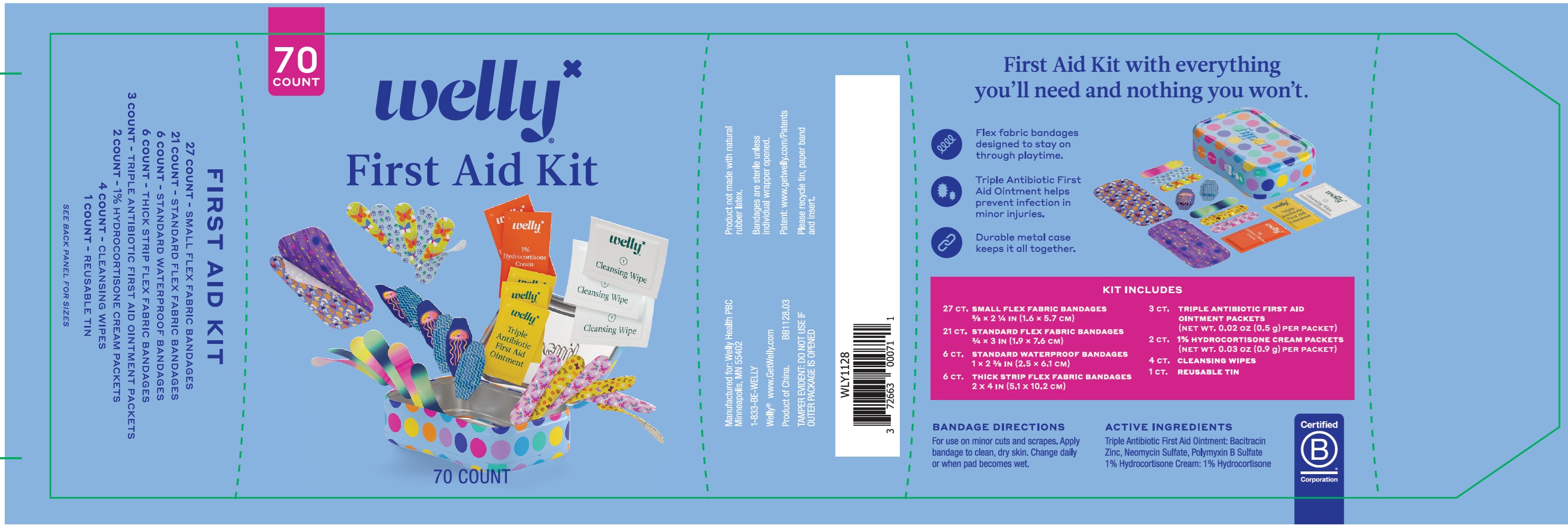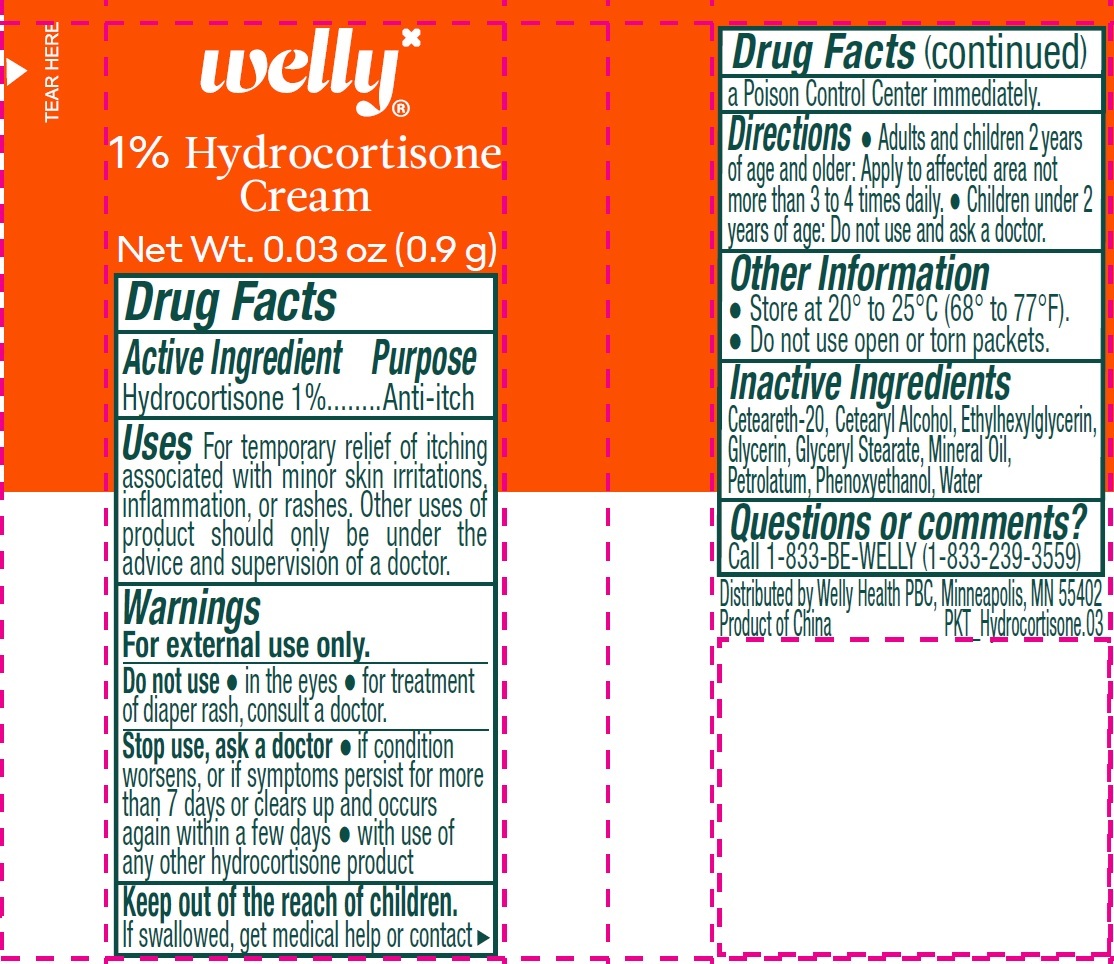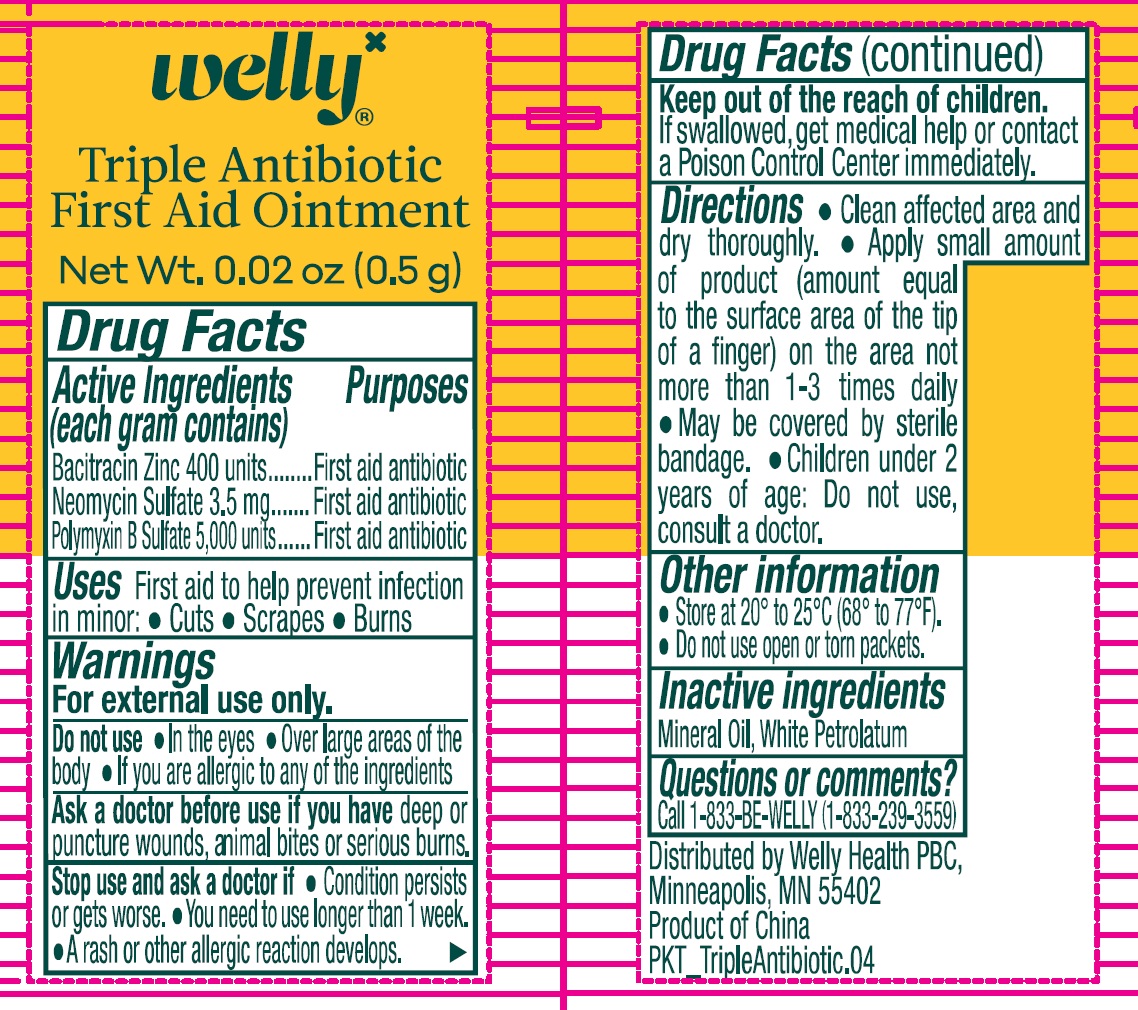 DRUG LABEL: Welly Polka First Aid Kit
NDC: 84956-009 | Form: KIT | Route: TOPICAL
Manufacturer: Dongguan Shenglian Tins Products Co., Ltd.
Category: otc | Type: HUMAN OTC DRUG LABEL
Date: 20251217

ACTIVE INGREDIENTS: HYDROCORTISONE 10 mg/1 g; BACITRACIN ZINC 400 [USP'U]/1 g; NEOMYCIN SULFATE 3.5 mg/1 g; POLYMYXIN B SULFATE 5000 [USP'U]/1 g
INACTIVE INGREDIENTS: CETOSTEARYL ALCOHOL; ETHYLHEXYLGLYCERIN; GLYCERIN; GLYCERYL MONOSTEARATE; MINERAL OIL; PETROLATUM; PHENOXYETHANOL; WATER; POLYOXYL 20 CETOSTEARYL ETHER; MINERAL OIL; WHITE PETROLATUM

Welly Polka First Aid Kit

Active Ingredient

Hydrocortisone 1%

Purpose

Anti-itch

Uses

For temporary relief of itching associated with minor skin irritations, inflammation, or rashes. Other uses of product should only be under the advice and supervision of a doctor.

Warnings

For external use only.

Do not use

● in the eyes ● for treatment of diaper rash, consult a doctor.

Stop use, ask a doctor

● if condition worsens, or if symptoms persist for more than 7 days or clears up and occurs again within a few days ● with use of any other hydrocortisone product

Keep out of the reach of children.

If swallowed, get medical help or contact a Poison Control Center immediately.

Directions

● Adults and children 2 years of age and older: Apply to affected area not more than 3 to 4 times daily. ● Children under 2 years of age: Do not use and ask a doctor.

Other Information

● Store at 20° to 25°C (68° to 77°F).
● Do not use open or torn packets.

Inactive Ingredients

Ceteareth-20, Cetearyl Alcohol, Ethylhexylglycerin, Glycerin, Glyceryl Stearate, Mineral Oil, Petrolatum, Phenoxyethanol, Water

Questions or comments?

Call 1-833-BE-WELLY (1-833-239-3559)

Active Ingredients (each gram contains)

Bacitracin Zinc 400 units

Neomycin Sulfate 3.5 mg

Polymyxin B Sulfate 5,000 units

Purposes

First aid antibiotic

Uses

First aid to help prevent infection in minor: ● Cuts ● Scrapes ● Burns

Warnings

For external use only.

Do not use

● In the eyes ● Over large areas of the body ● If you are allergic to any of the ingredients

Ask a doctor before use if you have

deep or puncture wounds, animal bites or serious burns.

Stop use and ask a doctor if

● Condition persists or gets worse. ● You need to use longer than 1 week. ● A rash or other allergic reaction develops.

Keep out of the reach of children.

If swallowed, get medical help or contact a Poison Control Center immediately.

Directions

● Clean affected area and dry thoroughly. ● Apply small amount of product (amount equal to the surface area of the tip of a finger) on the area not more than 1-3 times daily ● May be covered by sterile bandage. ● Children under 2 years of age: Do not use, consult a doctor.

Other information

● Store at 20° to 25°C (68° to 77°F).
● Do not use open or torn packets.

Inactive ingredients

Mineral Oil, White Petrolatum

Questions or comments?

Call 1-833-BE-WELLY (1-833-239-3559)